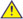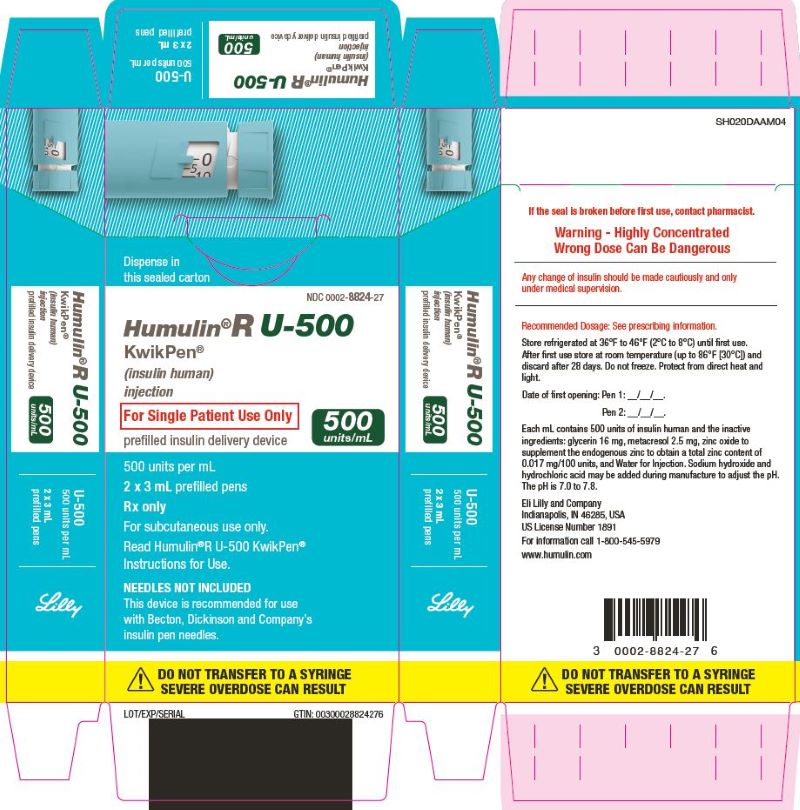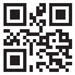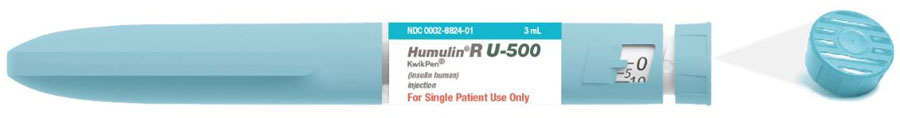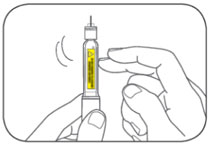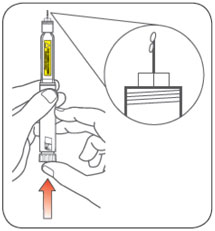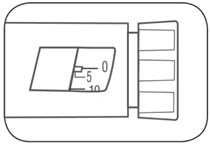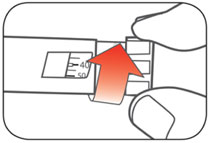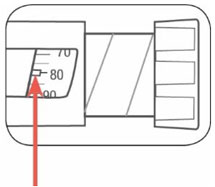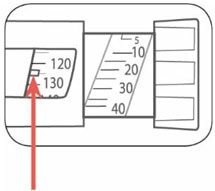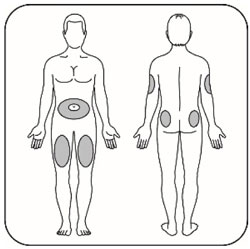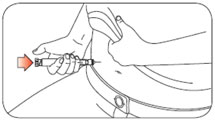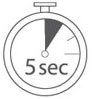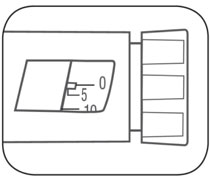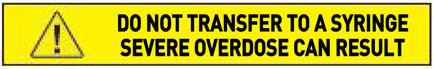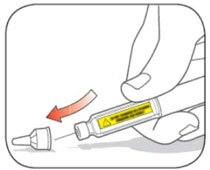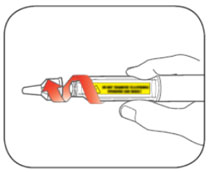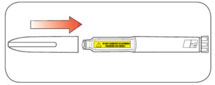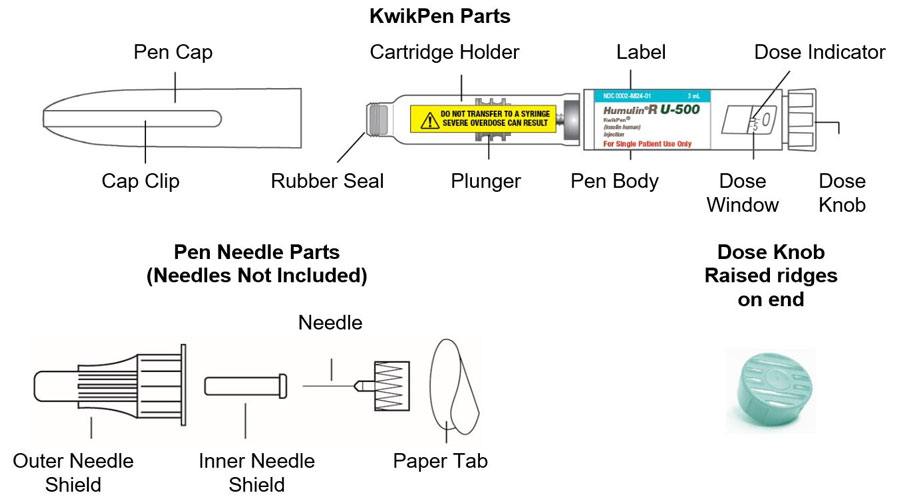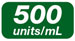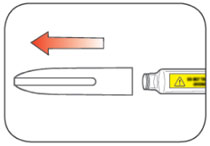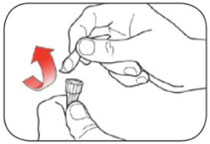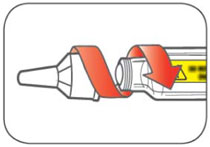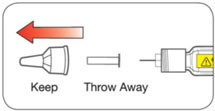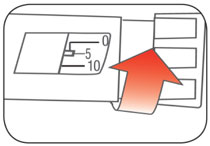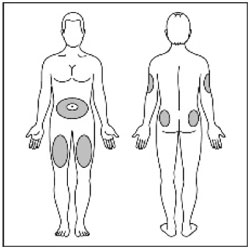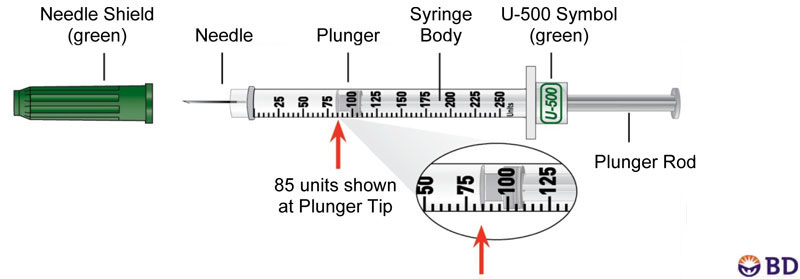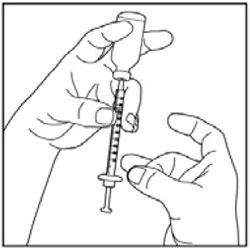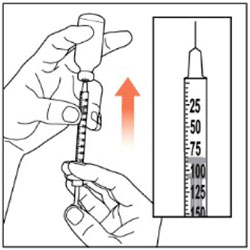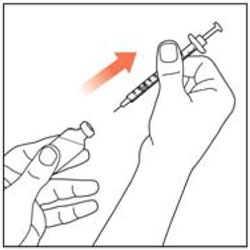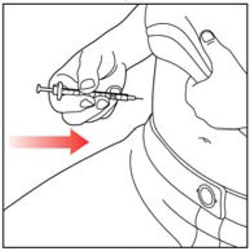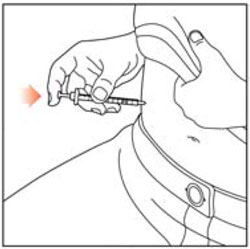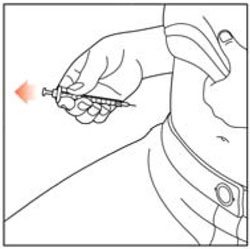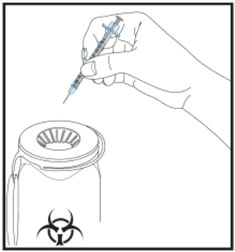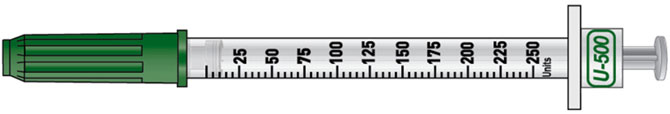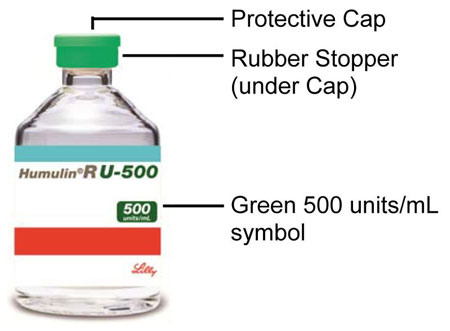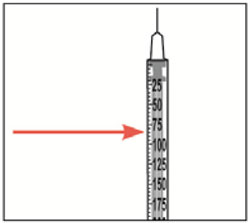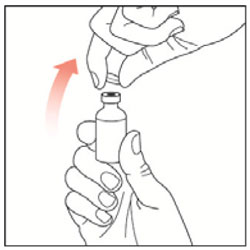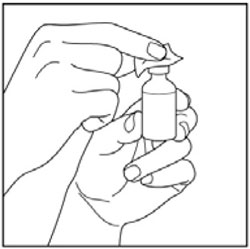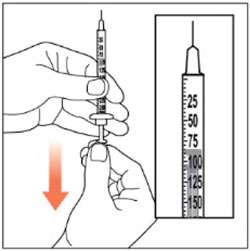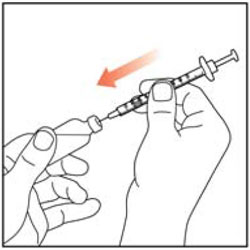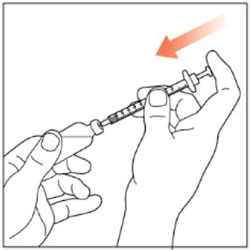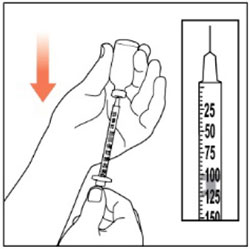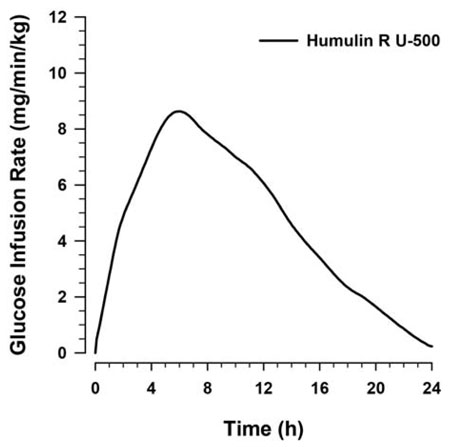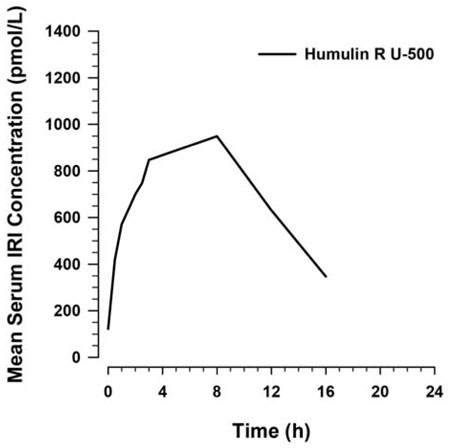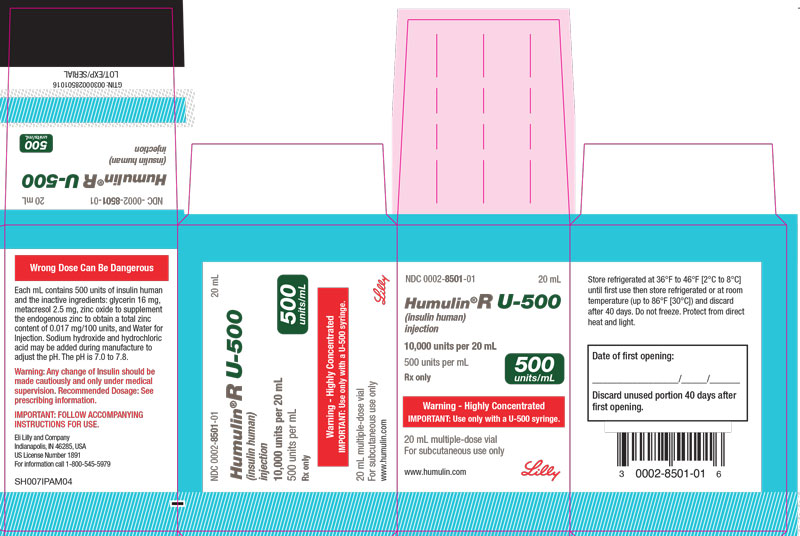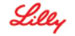 DRUG LABEL: Humulin
NDC: 0002-8501 | Form: INJECTION, SOLUTION
Manufacturer: Eli Lilly and Company
Category: prescription | Type: HUMAN PRESCRIPTION DRUG LABEL
Date: 20240222

ACTIVE INGREDIENTS: Insulin human 500 [iU]/1 mL
INACTIVE INGREDIENTS: Glycerin 16 mg/1 mL; Metacresol 2.5 mg/1 mL; Zinc 0.085 mg/1 mL; Water; Hydrochloric acid; Sodium hydroxide

HIGHLIGHTS OF PRESCRIBING INFORMATION

These highlights do not include all the information needed to use HUMULIN R U-500 safely and effectively. See full prescribing information for HUMULIN R U-500.
HUMULIN R U-500 (insulin human) injection, for subcutaneous use
Initial U.S. Approval: 1994

1 INDICATIONS AND USAGE

HUMULIN® R U-500 is a concentrated human insulin indicated to improve glycemic control in adults and pediatric patients with diabetes mellitus requiring more than 200 units of insulin per day. (1)

Limitation of Use: The safety and efficacy of HUMULIN R U-500 used in combination with other insulins has not been determined. The safety and efficacy of HUMULIN R U-500 delivered by continuous subcutaneous infusion has not been determined. (1.1)

2 DOSAGE AND ADMINISTRATION

- Adhere to administration instructions to reduce the risk of dosing errors. (2.1, 2.3, 2.4, 5.1)
- HUMULIN R U-500 is available as a single-patient-use KwikPen or multiple-dose vial. Patients using the vial must be prescribed the U-500 insulin syringe to avoid medication errors. (2.1)
- Individualize dose of HUMULIN R U-500 based on metabolic needs, blood glucose monitoring results and glycemic control goal. (2.2)
- Administer HUMULIN R U-500 subcutaneously two or three times daily 30 minutes before a meal into the thigh, upper arm, abdomen, or buttocks. Rotate injection sites to reduce risk of lipodystrophy and localized cutaneous amyloidosis. (2.1, 2.2)
- Do NOT mix HUMULIN R U-500 with other insulins. (2.1)
- Do NOT administer HUMULIN R U-500 intravenously (2.1)
- Do NOT perform dose conversion when using the HUMULIN R U-500 KwikPen. The dose window of the HUMULIN R U-500 KwikPen shows the number of units of HUMULIN R U-500 to be injected. (2.3)
- Do NOT transfer HUMULIN R U-500 from the HUMULIN R U-500 KwikPen into any syringe. (2.3)
- Do NOT perform dose conversion when using a U-500 insulin syringe. Use only a U-500 insulin syringe with the HUMULIN R U-500 vial. (2.4)

3 DOSAGE FORMS AND STRENGTHS

Injection: 500 units/mL (U-500) available as: (3)

- 3 mL single-patient-use HUMULIN® R U-500 KwikPen® prefilled pen (containing 1,500 units of insulin)
- 20 mL multiple-dose vial (containing 10,000 units of insulin)

4 CONTRAINDICATIONS

- Do not use during episodes of hypoglycemia. (4)
- Do not use in patients with hypersensitivity to HUMULIN R U-500 or any of its excipients. (4)

5 WARNINGS AND PRECAUTIONS

- Hyperglycemia, Hypoglycemia or Death due to Dosing Errors with Vial Presentation: Can be life-threatening. Overdose has occurred as a result of dispensing, prescribing or administration errors. Attention to details at all levels is required to prevent these errors. (2.1, 2.3, 2.4, 5.1)
- Never share a HUMULIN R U-500 KwikPen or U-500 insulin syringe between patients, even if the needle is changed. (5.2)
- Hyperglycemia or Hypoglycemia with Changes in Insulin Regimen: Make changes to a patient's insulin regimen (e.g., insulin strength, manufacturer, type, injection site or method of administration) under close medical supervision with increased frequency of blood glucose monitoring. (5.3)
- Hypoglycemia: May be life-threatening. Increase monitoring with changes to: insulin dosage, co-administered glucose lowering medications, meal pattern, physical activity; and in patients with renal impairment or hepatic impairment or hypoglycemia unawareness. (5.4)
- Hypersensitivity Reactions: Severe, life-threatening, generalized allergy, including anaphylaxis, can occur. Discontinue HUMULIN R U-500, monitor, and treat if indicated. (5.5)
- Hypokalemia: May be life-threatening. Monitor potassium levels in patients at risk for hypokalemia and treat if indicated. (5.6)
- Fluid Retention and Heart Failure with Concomitant Use of Thiazolidinediones (TZDs): Observe for signs and symptoms of heart failure; consider dosage reduction or discontinuation if heart failure occurs. (5.7)

6 ADVERSE REACTIONS

Adverse reactions associated with HUMULIN R U-500 include hypoglycemia, allergic reactions, injection site reactions, lipodystrophy, pruritus, and rash. (6)

To report SUSPECTED ADVERSE REACTIONS, contact Eli Lilly and Company at 1-800-LillyRx (1-800-545-5979) or FDA at 1-800-FDA-1088 or www.fda.gov/medwatch.

7 DRUG INTERACTIONS

- Drugs that Affect Glucose Metabolism: Adjustment of insulin dosage may be needed. (7)
- Antiadrenergic Drugs (e.g., beta-blockers, clonidine, guanethidine, and reserpine): Signs and symptoms of hypoglycemia may be reduced or absent. (5.3, 7)

FULL PRESCRIBING INFORMATION

1 INDICATIONS AND USAGE

HUMULIN R U-500 is a concentrated human insulin indicated to improve glycemic control in adult and pediatric patients with diabetes mellitus requiring more than 200 units of insulin per day.

1.1 Limitation of Use

The safety and efficacy of HUMULIN R U-500 used in combination with other insulins has not been determined.

The safety and efficacy of HUMULIN R U-500 delivered by continuous subcutaneous infusion has not been determined.

2 DOSAGE AND ADMINISTRATION

2.1 Important Administration Instructions

- Prescribe HUMULIN R U-500 ONLY to patients who require more than 200 units of insulin per day.
- HUMULIN R U-500 is available as a single-patient-use KwikPen or multiple-dose vial. Patients using the vial must be prescribed the U-500 insulin syringe to avoid medication errors.
- Instruct patients using the vial presentation to use only a U-500 insulin syringe and on how to correctly draw the prescribed dose of HUMULIN R U-500 into the U-500 insulin syringe. Confirm that the patient has understood these instructions and can correctly draw the prescribed dose of HUMULIN R U-500 with their syringe [see Dosage and Administration (2.4) and Warnings and Precautions (5.1)].
- Instruct patients to always check the insulin label before administration to confirm the correct insulin product is being used [see Warnings and Precautions (5.1)].
- Inspect HUMULIN R U-500 visually for particulate matter and discoloration. Only use HUMULIN R U-500 if the solution appears clear and colorless.
- Instruct patients to inject HUMULIN R U-500 subcutaneously into the thigh, upper arm, abdomen, or buttocks.
- Rotate injection sites within the same region from one injection to the next to reduce the risk of lipodystrophy and localized cutaneous amyloidosis. Do not inject into areas of lipodystrophy or localized cutaneous amyloidosis [see Warnings and Precautions (5.3) and Adverse Reactions (6)].
- During changes to a patient's insulin regimen, increase the frequency of blood glucose monitoring [see Warnings and Precautions (5.3)].
- Use HUMULIN R U-500 KwikPen with caution in patients with visual impairment that may rely on audible clicks to dial their dose.
- DO NOT administer HUMULIN R U-500 intravenously.
- DO NOT dilute or mix HUMULIN R U-500 with any other insulin products or solutions.

2.2 Dosing Instructions

- Instruct patients to inject HUMULIN R U-500 subcutaneously usually two or three times daily approximately 30 minutes before meals.
- Individualize and titrate the dosage of HUMULIN R U-500 based on the patient's metabolic needs, blood glucose monitoring results, and glycemic control goal.
- Dosage adjustments may be needed with changes in physical activity, changes in meal patterns (i.e., macronutrient content or timing of food intake), changes in renal or hepatic function, changes in medications or during acute illness to minimize the risk of hypoglycemia or hyperglycemia [see Warnings and Precautions (5.3)].

2.3 Delivery of HUMULIN R U-500 Using the HUMULIN R U-500 Disposable Prefilled KwikPen Device

- The HUMULIN R U-500 KwikPen dials in 5 unit increments and delivers a maximum dose of 300 units per injection.
- DO NOT perform dose conversion when using the HUMULIN R U-500 KwikPen. The dose window of the HUMULIN R U-500 KwikPen shows the number of units of HUMULIN R U-500 to be injected and NO dose conversion is required.
- DO NOT transfer HUMULIN R U-500 from the HUMULIN R U-500 KwikPen into any syringe for administration as overdose and severe hypoglycemia can occur [see Warnings and Precautions (5.4)].

2.4 Delivery of HUMULIN R U-500 Using the Vial Presentation and the U-500 Insulin Syringe

- DO NOT perform dose conversion when using a U-500 insulin syringe. The markings on the U-500 insulin syringe show the number of units of HUMULIN R U-500 to be injected.
- Each marking on the syringe represents 5 units of insulin.
- Prescribe patients a U-500 insulin syringe to administer HUMULIN R U-500 from the vial to avoid administration errors. DO NOT use any other type of syringe [see Warnings and Precautions (5.1)].

3 DOSAGE FORMS AND STRENGTHS

Injection: 500 units/mL (U-500) clear, colorless solution available as:

- 3 mL single-patient-use HUMULIN R U-500 KwikPen prefilled pen (containing 1,500 units of insulin)
- 20 mL multiple-dose vial (containing 10,000 units of insulin)

4 CONTRAINDICATIONS

HUMULIN R U-500 is contraindicated:

- During episodes of hypoglycemia [see Warnings and Precautions (5.4)]
- In patients who are hypersensitive to HUMULIN R U-500 or any of its excipients [see Warnings and Precautions (5.5)]

5 WARNINGS AND PRECAUTIONS

5.1 Hyperglycemia, Hypoglycemia or Death Due to Dosing Errors with the Vial Presentation

Medication errors associated with the HUMULIN R U-500 vial presentation resulting in patients experiencing hyperglycemia, hypoglycemia or death have been reported. The majority of errors occurred due to errors in dispensing, prescribing or administration. Attention to details at all levels may prevent these errors.

Dispensing Errors

Instruct patients to always inspect insulin vials to confirm that the correct insulin is dispensed including the correct insulin brand and concentration.

The HUMULIN R U-500 vial, which contains 20 mL, has a band of aqua coloring, a 500 units/mL concentration statement consisting of white lettering on a green rectangular background, and a green “U-500” statement prominently displayed next to the trade name. Additionally, the vial has a green flip top and a red warning on the front panel describing the highly concentrated dose and a statement advising use with only U-500 insulin syringes.

Prescribing Errors

Dosing errors have occurred when the HUMULIN R U-500 dose was administered with syringes other than a U-500 insulin syringe. Patients should be prescribed U-500 syringes for use with the HUMULIN R U-500 vials. The prescribed dose of HUMULIN R U-500 should always be expressed in units of insulin [see Dosage and Administration (2.4)].

Administration Errors

Instruct patients to always check the insulin label before each injection.

Use only a U-500 insulin syringe with HUMULIN R U-500 to avoid administration errors. Do not use any other type of syringe to administer Humulin R U-500. Adhere to administration instructions [see Dosage and Administration (2.1, 2.4)].

Instruct the patient to inform hospital or emergency department staff of the dose of HUMULIN R U-500 prescribed, in the event of a future hospitalization or visit to the emergency department.

5.2 Never Share a HUMULIN R U-500 KwikPen or U-500 Insulin Syringe Between Patients

HUMULIN R U-500 KwikPens should never be shared between patients, even if the needle is changed. Patients using HUMULIN R U-500 vials should never share needles or U-500 insulin syringes with another person. Sharing poses a risk for transmission of blood-borne pathogens.

5.3 Hyperglycemia or Hypoglycemia with Changes in Insulin Regimen

Changes in an insulin regimen (e.g., insulin strength, manufacturer, type, injection site or method of administration) may affect glycemic control and predispose to hypoglycemia [see Warnings and Precautions (5.4)] or hyperglycemia. Repeated insulin injections into areas of lipodystrophy or localized cutaneous amyloidosis have been reported to result in hyperglycemia; and a sudden change in the injection site (to an unaffected area) has been reported to result in hypoglycemia [see Adverse Reactions (6)].

Make any changes to a patient's insulin regimen under close medical supervision with increased frequency of blood glucose monitoring. Advise patients who have repeatedly injected into areas of lipodystrophy or localized cutaneous amyloidosis to change the injection site to unaffected areas and closely monitor for hypoglycemia. For patients with type 2 diabetes, adjustments in concomitant oral anti-diabetic treatment may be needed.

5.4 Hypoglycemia

Hypoglycemia is the most common adverse reaction associated with insulins, including HUMULIN R U-500. Severe hypoglycemia can cause seizures, may be life-threatening or cause death. Severe hypoglycemia may develop as long as 18 to 24 hours after an injection of HUMULIN R U-500. Hypoglycemia can impair concentration ability and reaction time; this may place the patient and others at risk in situations where these abilities are important (e.g., driving, or operating other machinery).

Hypoglycemia can happen suddenly and symptoms may differ in each patient and change over time in the same patient. Symptomatic awareness of hypoglycemia may be less pronounced in patients with longstanding diabetes, in patients with diabetic neuropathy, in patients using medications that block the sympathetic nervous system (e.g., beta-blockers) [see Drug Interactions (7.3, 7.4)], or in patients who experience recurrent hypoglycemia.

Risk Factors for Hypoglycemia

The timing of hypoglycemia usually reflects the time-action profile of the administered insulin formulation. As with all insulin preparations, the glucose lowering effect time course of HUMULIN R U-500 may vary in different individuals or at different times in the same individual and depends on many conditions, including the area of injection as well as the injection site blood supply and temperature.

Other factors which may increase the risk of hypoglycemia include changes in meal pattern (e.g., macronutrient content or timing of meals), changes in level of physical activity, or changes to concomitant drugs [see Drug Interactions (7.1, 7.2, 7.3, 7.4)]. Patients with renal or hepatic impairment may be at higher risk of hypoglycemia [see Use in Specific Populations (8.6, 8.7)].

Risk Mitigation Strategies for Hypoglycemia

Patients and caregivers must be educated to recognize and manage hypoglycemia. Self-monitoring of blood glucose plays an essential role in the prevention and management of hypoglycemia. In patients at higher risk for hypoglycemia and patients who have reduced symptomatic awareness of hypoglycemia, increased frequency of blood glucose monitoring is recommended. To minimize the risk of hypoglycemia do not administer HUMULIN R U-500 intravenously or in an insulin pump or dilute or mix HUMULIN R U-500 with any other insulin products or solutions [see Dosage and Administration (2.1)].

5.5 Hypersensitivity Reactions

Severe, life-threatening, generalized allergy, including anaphylaxis, can occur with insulins, including HUMULIN R U-500. If hypersensitivity reactions occur, discontinue HUMULIN R U-500; treat per standard of care and monitor until symptoms and signs resolve [see Adverse Reactions (6)].

5.6 Hypokalemia

All insulins, including HUMULIN R U-500, cause a shift in potassium from the extracellular to intracellular space, possibly leading to hypokalemia. Untreated hypokalemia may cause respiratory paralysis, ventricular arrhythmia, and death. Use caution in patients who may be at risk for hypokalemia (e.g., patients using potassium-lowering medications, patients taking medications sensitive to serum potassium concentrations).

5.7 Fluid Retention and Heart Failure with Concomitant Use of PPAR-gamma Agonists

Thiazolidinediones (TZDs), which are peroxisome proliferator-activated receptor (PPAR)-gamma agonists, can cause dose-related fluid retention, when used in combination with insulin. Fluid retention may lead to or exacerbate heart failure. Patients treated with insulin, including HUMULIN R U-500, and a PPAR-gamma agonist should be observed for signs and symptoms of heart failure. If heart failure develops, it should be managed according to current standards of care, and discontinuation or dose reduction of the PPAR-gamma agonist must be considered.

6 ADVERSE REACTIONS

The following adverse reactions are discussed elsewhere:

- Hypoglycemia [see Warnings and Precautions (5.4)].
- Hypersensitivity Reactions [see Warnings and Precautions (5.5)].
- Hypokalemia [see Warnings and Precautions (5.6)].

The following additional adverse reactions have been identified during post-approval use of HUMULIN R U-500. Because these reactions are reported voluntarily from a population of uncertain size, it is not always possible to reliably estimate their frequency or to establish a causal relationship to drug exposure.

Hypoglycemia

Hypoglycemia is the most commonly observed adverse reaction in patients using insulin, including HUMULIN R U-500.

Allergic Reactions

Severe, life-threatening, generalized allergy, including anaphylaxis, generalized skin reactions, rash, angioedema, bronchospasm, hypotension, and shock may occur with insulins, including HUMULIN R U-500 and may be life threatening.

Lipodystrophy

Long-term use of insulin, including HUMULIN R U-500, can cause lipodystrophy at the site of repeated insulin injections. Lipodystrophy includes lipohypertrophy (thickening of adipose tissue) and lipoatrophy (thinning of adipose tissue) and may affect insulin absorption. Rotate insulin injections sites within the same region to reduce the risk of lipodystrophy [see Dosage and Administration (2.1)].

Localized Cutaneous Amyloidosis

Localized cutaneous amyloidosis at the injection site has occurred. Hyperglycemia has been reported with repeated insulin injections into areas of localized cutaneous amyloidosis; hypoglycemia has been reported with a sudden change to an unaffected injection site.

Injection Site Reactions

Patients taking HUMULIN R U-500 may experience injection site reactions, including injection site hematoma, pain, hemorrhage, erythema, nodules, swelling, discoloration, pruritus, warmth, and injection site mass.

Weight Gain

Weight gain can occur with insulins, including HUMULIN R U-500, and has been attributed to the anabolic effects of insulin.

Peripheral Edema

Insulins, including HUMULIN R U-500, may cause sodium retention and edema, particularly if previously poor metabolic control is improved by intensified insulin therapy.

Immunogenicity

As with all therapeutic proteins, insulin administration may cause anti-insulin antibodies to form. The presence of antibodies that affect clinical efficacy may necessitate dose adjustments to correct for tendencies toward hyper- or hypoglycemia.

The incidence of antibody formation with HUMULIN R U-500 is unknown.

7 DRUG INTERACTIONS

Table 1: Clinically Significant Drug Interactions with HUMULIN R U-500
Drugs That May Increase the Risk of Hypoglycemia
Drugs: | Antidiabetic agents, ACE inhibitors, angiotensin II receptor blocking agents, disopyramide, fibrates, fluoxetine, monoamine oxidase inhibitors, pentoxifylline, pramlintide, salicylates, somatostatin analog (e.g., octreotide), and sulfonamide antibiotics.
Intervention: | Dose adjustment and increased frequency of glucose monitoring may be required when HUMULIN R U-500 is co-administered with these drugs.
Drugs That May Decrease the Blood Glucose Lowering Effect of HUMULIN R U 500
Drugs: | Atypical antipsychotics (e.g., olanzapine and clozapine), corticosteroids, danazol, diuretics, estrogens, glucagon, isoniazid, niacin, oral contraceptives, phenothiazines, progestogens (e.g., in oral contraceptives), protease inhibitors, somatropin, sympathomimetic agents (e.g., albuterol, epinephrine, terbutaline), and thyroid hormones.
Intervention: | Dose adjustment and increased frequency of glucose monitoring may be required when HUMULIN R U-500 is co-administered with these drugs.
Drugs That May Increase or Decrease the Blood Glucose Lowering Effect of HUMULIN R U 500
Drugs: | Alcohol, beta-blockers, clonidine, and lithium salts. Pentamidine may cause hypoglycemia, which may sometimes be followed by hyperglycemia.
Intervention: | Dose adjustment and increased frequency of glucose monitoring may be required when HUMULIN R U-500 is co-administered with these drugs.
Drugs That May Blunt Signs and Symptoms of Hypoglycemia
Drugs: | Beta-blockers, clonidine, guanethidine and reserpine
Intervention: | Increased frequency of glucose monitoring may be required when HUMULIN R U-500 is co-administered with these drugs.

8 USE IN SPECIFIC POPULATIONS

8.1 Pregnancy

Risk Summary

Available data from published studies over decades have not established an association with human insulin use during pregnancy and major birth defects, miscarriage, or adverse maternal or fetal outcomes (see Data). There are risks to the mother and fetus associated with poorly controlled diabetes in pregnancy (see Clinical Considerations). Animal reproduction studies were not performed.

The estimated background risk of major birth defects is 6-10% in women with pre-gestational diabetes with a HbA1c >7% and has been reported to be as high as 20-25% in women with a HbA1c >10%. The estimated background risk of miscarriage for the indicated population is unknown. In the U.S. general population, the estimated background risk of major birth defects and miscarriage in clinically recognized pregnancies is 2-4% and 15-20%, respectively.

Clinical Considerations

Disease-associated maternal and/or embryo/fetal risk

Poorly controlled diabetes in pregnancy increases the maternal risk for diabetic ketoacidosis, pre-eclampsia, spontaneous abortions, preterm delivery, and delivery complications. Poorly controlled diabetes increases the fetal risk for major birth defects, stillbirth, and macrosomia-related morbidity.

Data

Human Data

While available studies cannot definitively establish the absence of risk, published data from retrospective studies, open-label, randomized, parallel studies and meta-analyses over decades have not established an association with human insulin use during pregnancy and major birth defects, miscarriage, or adverse maternal or fetal outcomes. All available studies have methodological limitations, including lack of blinding, unclear methods or randomization, and small sample size.

8.2 Lactation

Risk Summary

Available data from published literature suggests that exogenous human insulin products, including HUMULIN R U-500, are transferred into human milk. There are no adverse reactions reported in breastfed infants in the literature. There are no data on the effects of exogenous human insulin products, including HUMULIN R U-500 on milk production. The developmental and health benefits of breastfeeding should be considered along with the mother's clinical need for HUMULIN R U-500 and any potential adverse effects on the breastfed child from HUMULIN R U-500 or from the underlying maternal condition.

8.4 Pediatric Use

The safety and effectiveness of HUMULIN R U-500 in pediatric patients with diabetes mellitus requiring more than 200 units of insulin per day to improve glycemic control have been established. Use of HUMULIN R U-500 for this indication is supported by evidence from studies with other insulin human in pediatric patients with type 1 diabetes mellitus and from studies in adults with diabetes mellitus. Standard precautions as applied to use of HUMULIN R U-500 in adults are appropriate for use in pediatric patients.

8.5 Geriatric Use

The effect of age on the pharmacokinetics and pharmacodynamics of HUMULIN R U-500 has not been studied. Caution should be exercised when HUMULIN R U-500 is administered to geriatric patients. In elderly patients with diabetes, the initial dosing, dose increments, and maintenance dosage should be conservative to avoid hypoglycemia.

8.6 Renal Impairment

Frequent glucose monitoring and insulin dose reduction may be required in patients with renal impairment.

8.7 Hepatic Impairment

Frequent glucose monitoring and insulin dose reduction may be required in patients with hepatic impairment.

10 OVERDOSAGE

Excess insulin administration may cause hypoglycemia and hypokalemia. Mild episodes of hypoglycemia usually can be treated with oral glucose. Adjustments in drug dosage, meal patterns, or exercise may be needed. More severe episodes with coma, seizure, or neurologic impairment may be treated with a glucagon product for emergency use or concentrated intravenous glucose. Sustained carbohydrate intake and observation may be necessary because hypoglycemia may recur after apparent clinical recovery. Hypokalemia must be corrected appropriately.

11 DESCRIPTION

Insulin human is produced by recombinant DNA technology utilizing a non-pathogenic laboratory strain of Escherichia coli and has the empirical formula C257H383N65O77S6 with a molecular weight of 5.808 kDa.

HUMULIN R U-500 (insulin human) injection is a sterile, aqueous, and colorless solution for subcutaneous use. HUMULIN R U-500 contains 500 units of insulin human in each milliliter. Each milliliter of HUMULIN R U-500 also contains glycerin (16 mg), metacresol (2.5 mg), zinc oxide to supplement the endogenous zinc to obtain a total zinc content of 0.017 mg/100 units, and Water for Injection. Sodium hydroxide and hydrochloric acid may be added during manufacture to adjust the pH. The pH is 7.0 to 7.8.

12 CLINICAL PHARMACOLOGY

12.1 Mechanism of Action

Regulation of glucose metabolism is the primary activity of insulins, including HUMULIN R U-500. Insulins lower blood glucose by stimulating peripheral glucose uptake by skeletal muscle and fat, and by inhibiting hepatic glucose production. Insulins inhibit lipolysis and proteolysis, and enhance protein synthesis.

12.2 Pharmacodynamics

In a euglycemic clamp study of 24 healthy obese subjects (BMI=30-39 kg/m^2), single doses of HUMULIN R U-500 at 50 units (0.4-0.6 unit/kg) and 100 units (0.8-1.3 unit/kg) resulted in a mean time of onset of action of less than 15 minutes at both doses and a mean duration of action of 21 hours (range 13-24 hours). The time action characteristics reflect both prandial and basal activity, consistent with clinical experience. This effect has been attributed to the high concentration of the preparation.

Figure 1 should be considered a representative example since the time course of action of insulin may vary in different individuals or within the same individual. The rate of insulin absorption and consequently the onset of activity is known to be affected by the site of injection, exercise, and other variables [see Warnings and Precautions (5.3)].

Figure 1: Mean Insulin Activity Versus Time Profiles After Subcutaneous Injection of a 100 U Dose of HUMULIN R U-500 in Healthy Obese Subjects

12.3 Pharmacokinetics

Absorption — In a euglycemic clamp study of 24 healthy obese subjects, the median peak insulin level occurred between 4 hours (50 unit dose) and 8 hours (100 unit dose) with a range of 0.5-8 hours.

Metabolism — The uptake and degradation of insulin occurs predominantly in liver, kidney, muscle, and adipocytes, with the liver being the major organ involved in the clearance of insulin.

Elimination — Mean apparent half-life after subcutaneous administration of single doses of 50 units and 100 units to healthy obese subjects (N≥21) was approximately 4.5 hours (range=1.9-10 hours) for HUMULIN R U-500.

Figure 2: Mean Serum Insulin Concentrations Versus Time After Subcutaneous Injection of a 100 U Dose of HUMULIN R U-500 Healthy Obese Subjects

13 NONCLINICAL TOXICOLOGY

13.1 Carcinogenesis, Mutagenesis, Impairment of Fertility

Carcinogenicity and fertility studies were not performed with HUMULIN R U-500 in animals. Biosynthetic human insulin was not genotoxic in the in vivo sister chromatid exchange assay and the in vitro gradient plate and unscheduled DNA synthesis assays.

16 HOW SUPPLIED/STORAGE AND HANDLING

16.1 How Supplied

HUMULIN R U-500 (500 units/mL) injection is available in a clear, colorless solution as:

2 x 3 mL single-patient-use HUMULIN R U-500 KwikPen | NDC 0002-8824-27
20 mL multiple-dose vial | NDC 0002-8501-01

The HUMULIN R U-500 KwikPen dials in 5 unit increments.

16.2 Storage and Handling

Dispense in the original sealed carton with the enclosed Instructions for Use.

Protect from heat and light. Do not freeze. Do not use if it has been frozen. Do not shake the vial. See Table 2 below for storage conditions.

Table 2: Storage Conditions for HUMULIN R U-500 Vials and Pens
 | Not In-use (Unopened) |  | In-use (Opened)
 | Room Temperature (up to 86°F [30°C]) | Refrigerated (36° to 46°F [2° to 8°C]) | Room Temperature (up to 86°F [30°C]) | Refrigerated (36° to 46°F [2° to 8°C])
20 mL multiple-dose viala | 40 days | Until expiration date | 40 days | 40 days
3 mL single-patient-use HUMULIN R U-500 KwikPenb | 28 days | Until expiration date | 28 days | Do not refrigerate.
a When stored at room temperature, HUMULIN R U-500 vial can only be used for a total of 40 days, including both not in-use (unopened) and in-use (opened) storage time.
b When stored at room temperature, HUMULIN R U-500 KwikPen can only be used for a total of 28 days, including both not in-use (unopened) and in-use (opened) storage time.

17 PATIENT COUNSELING INFORMATION

See FDA-approved patient labeling.

Patients should be counseled that HUMULIN R U-500 is a 5-times concentrated insulin product. Extreme caution must be observed in the measurement of dosage because inadvertent overdose may result in serious adverse reaction or life-threatening hypoglycemia. Accidental mix-ups between insulin products have been reported. To avoid medication errors between HUMULIN R U-500 and other insulins, patients should be instructed to always check the insulin label before each injection [see Warnings and Precautions (5.1)].

If using the HUMULIN R U-500 KwikPen, patients should be counseled to dial and dose the prescribed number of units of insulin (no dose conversion is required) [see Dosage and Administration (2.3)].

When using HUMULIN R U-500 from a vial, patients should be counseled to use only a U-500 insulin syringe and be informed that no dose conversion is required [see Dosage and Administration (2.4)].

Patients should be instructed on self-management procedures including glucose monitoring, proper injection technique, and management of hypoglycemia and hyperglycemia, especially at initiation of HUMULIN R U-500 therapy. Patients must be instructed on handling of special situations such as intercurrent conditions (illness, stress, or emotional disturbances), an inadequate or skipped insulin dose, inadvertent administration of an increased insulin dose, inadequate food intake, and skipped meals. Advise patients that changes in insulin regimen can predispose to hyperglycemia or hypoglycemia and that changes in insulin regimen should be made under close medical supervision. Refer patients to the HUMULIN R U-500 Patient Information Leaflet for additional information [see Warnings and Precautions (5)].

Do not dilute or mix HUMULIN R U-500 with any other insulin products or solutions [see Dosage and Administration (2.1)].

Literature Revised: February 2024

Manufactured by:
Eli Lilly and Company,
Indianapolis, IN 46285, USA
US License Number 1891
Copyright © 1997, 2024, Eli Lilly and Company. All rights reserved.

LINR500-0010-USPI-20240222

Patient Information
Humulin® (HU-mu-lin) R U-500
(insulin human)
injection, for subcutaneous use
U-500 (500 units/mL)

Do not share your Humulin R U-500 KwikPen or U-500 insulin syringes with other people, even if the needle has been changed. You may give other people a serious infection or get a serious infection from them.
What is Humulin R U-500?

- Humulin R U-500 is a man-made insulin that is used to control high blood sugar in adults and children with diabetes mellitus who need more than 200 units of insulin in a day.
- Humulin R U-500 contains 5 times as much insulin (500 units/mL) in 1 mL as Humulin R U-100 (100 units/mL).
- It is not known if Humulin R U-500 is safe and effective when used in combination with other insulins.
- It is not known if Humulin R U-500 is safe and effective when given by continuous subcutaneous infusion.

Who should not take Humulin R U-500?
Do not take Humulin R U-500 if you:

- are having an episode of low blood sugar (hypoglycemia).
- have an allergy to human insulin or any of the ingredients in Humulin R U-500. See the end of this Patient Information leaflet for a complete list of ingredients in Humulin R U-500.

What should I tell my healthcare provider before using Humulin R U-500?
Before using Humulin R U-500, tell your healthcare provider about all your medical conditions including, if you:

- have liver or kidney problems.
- take other medicines, especially ones called TZDs (thiazolidinediones).
- have heart failure or other heart problems. If you have heart failure, it may get worse while you take TZDs with Humulin R U-500.
- are pregnant, planning to become pregnant. Talk with your healthcare provider about the best way to control your blood sugar if you plan to become pregnant or while you are pregnant.
- are breast-feeding or plan to breastfeed. Humulin R U-500 may pass into your breast milk. Talk with your healthcare provider about the best way to feed your baby while using HUMULIN R U-500.

Tell your healthcare provider about all the medicines you take, including prescription and over-the-counter medicines, vitamins, or herbal supplements.
Before you start using Humulin R U-500, talk to your healthcare provider about low blood sugar and how to manage it.

How should I use Humulin R U-500?

- Read the detailed Instructions for Use that come with your Humulin R U-500.
- Use Humulin R U-500 exactly as your healthcare provider tells you to. Your healthcare provider should tell you how much Humulin R U-500 to use and when to use it.
- Know the dose of Humulin R U-500 you use. Do not change the dose of Humulin R U-500 you use unless your healthcare provider tells you to.
- Check your insulin label each time you give your injection to make sure you are using the correct insulin.
- When using the Humulin R U-500 KwikPen: The Humulin R U-500 KwikPen is specially made to dial and deliver doses of Humulin R U-500 insulin. Do not use any syringe to remove Humulin R U-500 from your Humulin R U-500 KwikPen. The markings on certain syringes will not measure your dose correctly. A severe overdose can happen, causing low blood sugar, which may put your life in danger.
- When using the Humulin R U-500 vial: There is a special U-500 insulin syringe to measure Humulin R U-500. Use only a U-500 insulin syringe to draw up and inject your Humulin R U-500. If you do not use the right syringe type, you may take the wrong dose of Humulin R U-500. This can cause you to have too low blood sugar (hypoglycemia) or too high blood sugar (hyperglycemia). Your healthcare provider should show you how to draw up Humulin R U-500.
- Use Humulin R U-500 30 minutes before eating a meal.
- Inject Humulin R U-500 under the skin (subcutaneously) of your upper legs (thighs), upper arms, buttocks or stomach area (abdomen). Do not use Humulin R U-500 in an insulin pump or inject Humulin R U-500 into your vein (intravenously).
- Do not mix Humulin R U-500 in the KwikPen or vial with any other type of insulin or liquid medicine.
- Change (rotate) your injection sites within the area you choose with each dose to reduce your risk of getting lipodystrophy (pits in skin or thickened skin) and localized cutaneous amyloidosis (skin with lumps) at the injection sites.
  - Do not use the exact same spot for each injection.
  - Do not inject where the skin has pits, is thickened, or has lumps.
  - Do not inject where the skin is tender, bruised, scaly or hard, or into scars or damaged skin.
- Check your blood sugar levels. Ask your healthcare provider what your blood sugars should be and when you should check your blood sugar levels.

Keep Humulin R U-500 and all medicines out of reach of children.

Your dose of Humulin R U-500 may need to change because of:
• change in level of physical activity or exercise, weight gain or loss, increased stress, illness, change in diet, or because of other medicines you take.

What should I avoid while using Humulin R U-500?
While using Humulin R U-500 do not:

- drive or operate heavy machinery, until you know how Humulin R U-500 affects you.
- drink alcohol or use over-the-counter medicines that contain alcohol.

What are the possible side effects of Humulin R U-500?
Humulin R U-500 may cause serious side effects that can lead to death, including:

- low blood sugar (hypoglycemia). Signs and symptoms of low blood sugar may include:
  - dizziness or lightheadedness, sweating, confusion, headache, blurred vision, slurred speech, shakiness, fast heartbeat, anxiety, irritability or mood changes, hunger.
  - your healthcare provider may prescribe a glucagon product for emergency use so that others can give you an injection if your blood sugar becomes too low (hypoglycemic) and you are unable to take sugar by mouth.
- severe allergic reaction (whole body reaction). Get medical help right away if you have any of these signs or symptoms of a severe allergic reaction:
  - a rash over your whole body, have trouble breathing, a fast heartbeat, or sweating.
- low potassium in your blood (hypokalemia).
- heart failure. Taking certain diabetes pills called thiazolidinediones or “TZDs” with Humulin R U-500 may cause heart failure in some people. This can happen even if you have never had heart failure or heart problems before. If you already have heart failure, it may get worse while you take TZDs with Humulin R U-500. Your healthcare provider should monitor you closely while you are taking TZDs with Humulin R U-500. Tell your healthcare provider if you have any new or worse symptoms of heart failure including:
  - shortness of breath, swelling of your ankles or feet, sudden weight gain

Treatment with TZDs and Humulin R U-500 may need to be adjusted or stopped by your healthcare provider if you have new or worse heart failure.
Get emergency medical help if you have:

- severe hypoglycemia needing hospitalization or emergency room care, and be sure to tell the hospital staff the units of Humulin R U-500 that your healthcare provider has prescribed for you.
- trouble breathing, shortness of breath, fast heartbeat, swelling of your face, tongue, or throat, sweating, extreme drowsiness, dizziness, confusion.

The most common side effects of Humulin R U-500 include:

- low blood sugar (hypoglycemia), allergic reactions including reactions at your injection site, skin thickening or pits at the injection site (lipodystrophy), itching, and rash.

These are not all of the possible side effects of Humulin R U-500. Call your doctor for medical advice about side effects. You may report side effects to FDA at 1-800-FDA-1088.

General Information about the safe and effective use of Humulin R U-500
Medicines are sometimes prescribed for purposes other than those listed in a Patient Information leaflet. Do not use Humulin R U-500 for a condition for which it was not prescribed. Do not give Humulin R U-500 to other people, even if they have the same symptoms you have. It may harm them.
This Patient Information leaflet summarizes the most important information about Humulin R U-500. If you would like more information, talk with your healthcare provider. You can ask your pharmacist or healthcare provider for information about Humulin R U-500 that is written for healthcare professionals. For more information go to www.humulin.com or call 1-800-545-5979.

What are the ingredients in Humulin R U-500?
Active ingredient: insulin human
Inactive ingredients: glycerin, metacresol, zinc oxide, and Water for Injection as inactive ingredients. Sodium hydroxide and hydrochloric acid may be added to adjust the pH.
Manufactured by: Eli Lilly and Company, Indianapolis, IN 46285, USA
US License Number 1891
For more information about Humulin R U-500 go to www.humulin.com.
Copyright © 2015, 2022, Eli Lilly and Company. All rights reserved.

This Patient Information has been approved by the U.S. Food and Drug Administration.

Revised: June 2022

LINR500-0006-PPI-20220627

Instructions for Use
Humulin® R U-500
(insulin human)
injection, for subcutaneous use
20 mL multiple-dose vial (500 units/mL)

Please read these instructions before use.

Warnings

- For your safety, always inject Humulin® R U-500 insulin with a U-500 syringe.
- If you use another kind of syringe, you may get a dangerous overdose.

U-500 syringe – for single injection only
The U-500 syringe has a green U-500 symbol and a green Needle Shield on the syringe.

Important Information

- Humulin R U-500 is a concentrated insulin.
- Know your dose. Your health care provider will tell you the number of insulin units that you should take.
- Always inject Humulin R U-500 insulin with a U-500 syringe. Other syringes will not measure your dose correctly.
- If you use the wrong syringe, you can give yourself a severe overdose. This can cause very low blood sugar, which may put your life in danger. For example, using a U-100 syringe can give you a 5 times overdose.
- If you do not have a U-500 syringe, you should contact your health care provider or pharmacist.

Additional Safety Information

- Each line on the U-500 syringe measures 5 units of U-500 insulin.
- You can give from 5 to 250 units in one injection.
- If your dose is more than 250 units, you will need to give more than 1 injection.
- Make sure you know how to draw up your dose with a U-500 syringe. If you need help, call your health care provider.
- Do not reuse your U-500 syringe.
- Do not share your U-500 syringes with other people. You may give other people a serious infection or get a serious infection from them.
- Do not mix Humulin R U-500 with other insulins in the same syringe.
- You can get more instructions by calling Lilly at 1-800-LillyRx (1-800-545-5979).

Supplies

- Humulin R U-500 multiple-dose vial
- U-500 Syringe (BD [Becton, Dickinson and Company] syringes recommended)
- 2 alcohol swabs
- 1 sharps container

Before You Start

- Check your vial. Make sure it says Humulin R U-500.
- Check the expiration date on the vial. Do not use it if it is expired. Throw away the opened vial after 40 days, even if there is still insulin left in the vial.
- See if the insulin in the vial is clear. Do not use if it is thick, cloudy, or colored or has solid particles.
- Make sure you have a new U-500 Syringe. Check for the green U-500 symbol and green Needle Shield.
- Check your supply. Make sure you have enough Humulin R U-500 insulin and U-500 syringes for several injections. Always reorder before you run out.
- Check with your health care provider if you have any questions.

Use only a U-500 syringe to inject Humulin R U-500 insulin

Prepare

- Wash your hands with soap and water.
- Always use a new syringe for each injection to help prevent infections and blocked needles.

Step 1:
Find the line on the U-500 syringe that matches your prescribed dose. This is your Dose Line.
Each line is 5 units.

(Example: Arrow shows
Dose Line at 85 units)

Step 2:
If you are using a new vial, pull off the plastic Protective Cap.
Do not remove the Rubber Stopper.

Step 3:
Wipe the Rubber Stopper with an alcohol swab.

Step 4:
Hold the syringe with the Needle pointing up. Pull down on the Plunger Rod until the Plunger Tip reaches your Dose Line.

(Example Dose:
85 units shown)

Step 5:
Push the Needle through the Rubber Stopper of the vial.

Step 6:
Push the Plunger all the way in. This puts air into the vial.

Step 7:
Turn the vial and syringe upside down and slowly pull the Plunger down until the Plunger Tip is past your Dose Line.

(Example Dose: 85 units
Plunger is shown at 100 units)

If there are air bubbles, tap the syringe gently a few times. This lets the air bubbles rise to the top.

Step 8:
Slowly push the Plunger up until the Plunger Tip reaches your Dose Line.
Check the syringe to make sure that you have the right dose.

(Example Dose: 85 units shown)

Step 9:
Pull the syringe out of the vial's Rubber Stopper.

Inject

- Inject your insulin exactly as your healthcare provider has shown you.
- Change (rotate) your injection sites within the area you choose for each dose to reduce your risk of getting lipodystrophy (pits in skin or thickened skin) and localized cutaneous amyloidosis (skin with lumps) at the injection sites. Do not inject where the skin has pits, is thickened, or has lumps. Do not inject where the skin is tender, bruised, scaly or hard, or into scars or damaged skin.

Step 10:
Choose your injection site.
Humulin R U-500 is injected under the skin (subcutaneously). You may inject into your stomach area, buttocks, upper legs, or upper arms.
Wipe the skin with an alcohol swab. Let the injection site dry before you inject your dose.

Step 11:
Insert the Needle into your skin.

Step 12:
Push down on the Plunger to inject your dose.
Then keep the Needle in your skin for at least 5 seconds, to make sure you have injected all of your dose.

Step 13:
Pull the Needle out of your skin.

- You may see blood after you take the Needle out of your skin. This is normal. Press the injection site lightly with a piece of gauze or an alcohol swab. Do not rub the area.
- Do not put the Needle Shield back on the Needle, because you may get a needle stick injury.

Disposal of used syringes

- Put your used syringes in a FDA-cleared sharps disposal container right away after use. Do not throw away (dispose of) syringes in your household trash.

- If you do not have a FDA-cleared sharps disposal container, you may use a household container that is:
  - made of a heavy-duty plastic,
  - can be closed with a tight-fitting, puncture-resistant lid, without sharps being able to come out,
  - upright and stable during use,
  - leak-resistant, and
  - properly labeled to warn of hazardous waste inside the container.
- When your sharps disposal container is almost full, you will need to follow your community guidelines for the right way to dispose of your sharps disposal container. There may be state or local laws about how you should throw away used needles and syringes. For more information about safe sharps disposal, and for specific information about sharps disposal in the state that you live in, go to the FDA's website at: http://www.fda.gov/safesharpsdisposal.
- Do not dispose of your used sharps disposal container in your household trash unless your community guidelines permit this. Do not recycle your used sharps disposal container.

Storage and Handling

- Keep away from heat and out of direct light.
- Do not shake the vial.

Unopened vials:

- Store unopened vials in the refrigerator.
- Do not freeze Humulin R U-500. If it has been frozen, do not use it.
- If unopened vials have been stored in the refrigerator, you may use them until the expiration date.

After the vial has been opened:

- Store opened vials in the refrigerator or at room temperature (up to 86°F [30°C]) for up to 40 days.
- Throw away the opened vial after 40 days, even if there is still insulin left in the vial.

General Information

- Always use a U-500 syringe to inject Humulin R U-500 insulin.
- Never use other syringes. The lines and numbers on other syringes will not measure your dose correctly.
- You can give yourself the wrong dose if you use any other syringe, such as a U-100, tuberculin or allergy syringe.
  For example, a U-100 syringe is made to measure U-100 insulin. If you use a U-100 Syringe for your U-500 dose, you can give yourself a 5 times overdose.
- Do not make any changes to your dose or the type of insulin you use unless you are told to do so by your health care provider.
- Keep your vials and syringes out of the sight and reach of children.

Frequently Asked Questions

- Why do I need to use a U-500 syringe?
  Humulin R U-500 insulin and a U-500 syringe work together to help you inject the correct dose. Using any other syringe may result in dosing mistakes. This may put your life in danger.
- Do I have to convert my Humulin R U-500 insulin dose when I use the U-500 syringe?
  No, you do not have to convert your dose. Your health care provider should tell you how much Humulin R U-500 insulin to take in units and when to take it. Your health care provider should show you how to draw up your dose using the U-500 syringe.
- What should I do if I run out of U-500 syringes?
  If you run out of U-500 syringes, do not use any other syringe to inject Humulin R U-500 insulin. Call your health care provider or pharmacist for help. You may also call Lilly at 1-800-Lilly-Rx (1-800-545-5979).

Where to get more information and help

- If you have any questions about Humulin R U-500 insulin or U-500 syringes, contact Lilly at 1-800-Lilly-Rx (1-800-545-5979).
- You can also call your health care provider or pharmacist.
- For more information on Humulin R U-500 insulin, go to www.humulin.com

Scan this code to launch the humulin.com website

These Instructions for Use have been approved by the U.S. Food and Drug Administration.

Humulin® is a trademark of Eli Lilly and Company.

Manufactured by:
Eli Lilly and Company, Indianapolis, IN 46285, USA
US License Number 1891

Copyright © 1996, 2022, Eli Lilly and Company. All rights reserved.

Literature revised: June 2022

LINR500VL-0004-IFU-20220627

Instructions for Use
HUMULIN® R U-500 KwikPen®

(insulin human)
injection, for subcutaneous use
3 mL single-patient-use pen (500 units/mL, U-500)

Important:

- Know your dose of HUMULIN R U-500 insulin. The Pen delivers your dose in insulin units. Insulin units may not be the same as syringe markings. Ask your health care provider what your dose should be for your Pen.
- Your HUMULIN® R U-500 KwikPen® (Pen) works differently from other pens. It dials 5 insulin units with each click. Do not count clicks of the dose knob to select your dose. You may get too much insulin or you may not get enough insulin.
- HUMULIN R U-500 is a concentrated insulin. Do not transfer HUMULIN R U-500 insulin from your Pen into a syringe. A severe overdose can happen, causing very low blood sugar, which may put your life in danger.

Read the Instructions for Use before you start taking HUMULIN R U-500 and each time you get another Pen. There may be new information. This information does not take the place of talking to your healthcare provider about your medical condition or your treatment.

Do not share your HUMULIN R U-500 Pen with other people, even if the needle has been changed. You may give other people a serious infection or get a serious infection from them.

HUMULIN R U-500 KwikPen (“Pen”) is a disposable single-patient-use prefilled pen containing 1500 units of HUMULIN R. You can give yourself more than 1 dose from the Pen. Each turn (click) of the Dose Knob dials 5 units of insulin. You can give from 5 to 300 units in a single injection. The plunger only moves a little with each injection, and you may not notice that it moves. The plunger will only reach the end of the cartridge when you have used all 1500 units in the Pen.

Inject HUMULIN R U-500 only with your Pen. Do not transfer insulin from your Pen to a syringe.

People who are blind or have vision problems should not use the Pen without help from a person trained to use the Pen.

How to recognize your HUMULIN R U-500 KwikPen

- Pen color: Aqua
- Dose Knob: Aqua with raised ridges on the end
- Label: HUMULIN R U-500 and 500 units/mL in a green box

Supplies needed to give your injection

- HUMULIN R U-500 KwikPen
- KwikPen compatible Needle (Becton, Dickinson and Company Pen Needles recommended)
- Alcohol swab

Preparing your Pen

- Wash your hands with soap and water.
- Check the Pen to make sure you are taking the right type of insulin. This is especially important if you use more than 1 type of insulin.
- Do not use your Pen past the expiration date printed on the Label or for more than 28 days after you first start using the Pen.
- Always use a new Needle for each injection to help prevent infections and blocked Needles. Do not reuse or share your needles with other people. You may give other people a serious infection or get a serious infection from them.

Step 1:

- Pull the Pen Cap straight off.
  - Do not remove the KwikPen Label.
- Wipe the Rubber Seal with an alcohol swab.
  HUMULIN R U-500 should look clear and colorless. Do not use if it is cloudy, colored, or has particles or clumps in it.

Step 2:

- Select a new Needle.
- Pull off the Paper Tab from the Outer Needle Shield.

Step 3:

- Push the capped Needle straight onto the Pen and twist the Needle on until it is tight.

Step 4:

- Pull off the Outer Needle Shield. Do not throw it away.
- Pull off the Inner Needle Shield and throw it away.

Priming your Pen

Prime before each injection.

- Priming your Pen means removing the air from the Needle and Cartridge that may collect during normal use and ensures that the Pen is working correctly.
- If you do not prime before each injection, you may get too much or too little insulin.

Step 5:

- To prime your pen, turn the Dose Knob to select 5 units.

Step 6:

- Hold your Pen with the Needle pointing up. Tap the Cartridge Holder gently to collect air bubbles at the top.

Step 7:

- Continue holding your Pen with Needle pointing up. Push the Dose Knob in until it stops, and “0” is seen in the Dose Window. Hold the Dose Knob in and count to 5 slowly.
  You should see insulin at the tip of the Needle.
  - If you do not see insulin, repeat priming steps 5 to 7, no more than 8 times.
  - If you still do not see insulin, change the Needle and repeat priming steps 5 to 7.

Small air bubbles are normal and will not affect your dose.

Selecting your dose

This Pen has been made to deliver the dose in insulin units that is shown in the Dose Window. Ask your healthcare provider what your dose should be for this Pen.

- You can give from 5 to 300 units in a single injection.
- If your dose is more than 300 units, you will need to give more than 1 injection.
  - If you need help with dividing up your dose the right way, ask your healthcare provider.
  - You must use a new Needle for each injection and repeat the priming step.

Step 8:

- Turn the Dose Knob to select the number of units you need to inject. The Dose Indicator should line up with your dose.
  - The Dose Knob clicks as you turn it. Each click of the Dose Knob dials 5 insulin units at a time.
  - Do not dial your dose by counting the clicks. You may dial the wrong dose. This may lead to you getting too much insulin or not enough insulin.
  - The dose can be corrected by turning the Dose Knob in either direction until the correct dose lines up with the Dose Indicator.
  - The even numbers (for example, 80) are printed on the dial.
  - The odd numbers (for example, 125) are shown as lines between the even numbers.
- Always check the number in the Dose Window to make sure you have dialed the correct dose.

Example: 80 units
shown in Dose Window

Example: 125 units
shown in Dose Window

- The Pen will not let you dial more than the number of units left in the Pen.
- If your dose is more than the number of units left in the Pen, you may either:
  - inject the amount left in your Pen and then use a new Pen to give the rest of your dose,
    or
  - get a new Pen and inject your full dose.
- It is normal to see a small amount of insulin left in the Pen that you cannot inject. Do not transfer this to a syringe. Severe overdose can happen.

Giving your injection

- Inject your insulin as your healthcare provider has shown you.
- Change (rotate) your injection sites within the area you choose for each dose to reduce your risk of getting lipodystrophy (pits in skin or thickened skin) and localized cutaneous amyloidosis (skin with lumps) at the injection sites. Do not inject where the skin has pits, is thickened, or has lumps. Do not inject where the skin is tender, bruised, scaly or hard, or into scars or damaged skin.
- Do not try to change your dose while injecting.

Step 9:

- Choose your injection site.
  HUMULIN is injected under the skin (subcutaneously) of your stomach area, buttocks, upper legs or upper arms.
- Wipe your skin with an alcohol swab, and let your skin dry before you inject your dose.

Step 10:

- Insert the Needle into your skin.
- Push the Dose Knob all the way in.

- Continue to hold the Dose Knob in and slowly count to 5 before removing the Needle.

Do not try to inject your insulin by turning the Dose Knob. You will not receive your insulin by turning the Dose Knob.

Step 11:

- Pull the Needle out of your skin.
  - A drop of insulin at the Needle tip is normal. It will not affect your dose.
- Check the number in the Dose Window.
  - If you see “0” in the Dose Window, you have received the full amount you dialed.
  - If you do not see “0” in the Dose Window, do not redial. Insert the Needle into your skin and finish your injection.
  - If you still do not think you received the full amount you dialed for your injection, do not start over or repeat your injection. Monitor your blood glucose as instructed by your healthcare provider.

The Plunger only moves a little with each injection, and you may not notice that it moves.
If you see blood after you take the Needle out of your skin, press the injection site lightly with a piece of gauze or an alcohol swab. Do not rub the area.

After your injection

Step 12:

- Carefully replace the Outer Needle Shield.

Step 13:

- Unscrew the capped Needle and throw it away (see Disposing of Pens and Needles section).
- Do not store the Pen with the Needle attached to prevent leaking, blocking the Needle, and air from entering the Pen.

Step 14:

- Replace the Pen Cap by lining up the Cap Clip with the Dose Indicator and pushing straight on.

Disposing of Pens and Needles

- Put your used Needles in a FDA-cleared sharps disposal container right away after use. Do not throw away (dispose of) loose Needles in your household trash.
- If you do not have a FDA-cleared sharps disposal container, you may use a household container that is:
  - made of a heavy-duty plastic,
  - can be closed with a tight-fitting, puncture-resistant lid, without sharps being able to come out,
  - upright and stable during use,
  - leak-resistant, and
  - properly labeled to warn of hazardous waste inside the container.
- When your sharps disposal container is almost full, you will need to follow your community guidelines for the right way to dispose of your sharps disposal container. There may be state or local laws about how you should throw away used needles and syringes. For more information about safe sharps disposal, and for specific information about sharps disposal in the state that you live in, go to the FDA's website at: http://www.fda.gov/safesharpsdisposal
- Do not dispose of your used sharps disposal container in your household trash unless your community guidelines permit this. Do not recycle your used sharps disposal container.
- The used Pen may be discarded in your household trash after you have removed the needle.

Storing your Pen

Unused Pens

- Store unused Pens in the refrigerator at 36°F to 46°F (2°C to 8°C).
- Do not freeze HUMULIN R U-500. Do not use if it has been frozen.
- Unused Pens may be used until the expiration date printed on the Label, if the Pen has been kept in the refrigerator.

In-use Pen

- Store the Pen you are currently using at room temperature up to 86°F (30°C). Keep away from heat and light.
- Throw away the Pen you are using after 28 days, even if it still has insulin left in it.

What you should know if you are switching to HUMULIN R U-500 KwikPen

Ask your healthcare provider what your dose should be for your Pen in insulin units. Always follow your healthcare provider's instructions for dosing.

If you are: | It is important to know:
Switching from HUMULIN R U-500 vial (and syringe) | Your Pen may measure your dose differently. The markings in the Dose Window may not be the same as the markings on the syringe you used in the past. If you were using the U-500 syringe to administer your dose, the markings on the syringe may be the same as the markings in the Pen Dose Window. Ask your healthcare provider what dose in insulin units you should dial on your Pen.
Switching from another type of insulin device or pen. | The HUMULIN R U-500 KwikPen is different from other pens. It dials 5 insulin units with each click of the Dose Knob. Do not select your dose by counting clicks. You may get too much insulin or you may not get enough insulin.

General information about the safe and effective use of your Pen

- Keep your Pen and Needles out of the sight and reach of children.
- Do not use your Pen if any part looks broken or damaged.
- Always carry an extra Pen in case yours is lost or damaged.

Troubleshooting

- If you cannot remove the Pen Cap, gently twist the cap back and forth, and then pull the cap straight off.
- If it is hard to push the Dose Knob:
  - Pushing the Dose Knob more slowly will make it easier to inject.
  - Your Needle may be blocked. Put on a new Needle and prime the Pen.
  - You may have dust, food, or liquid inside the Pen. Throw the Pen away and get a new Pen.

If you have any questions or problems with your HUMULIN R U-500 KwikPen, contact Lilly at 1-800-LillyRx (1-800-545-5979) or call your healthcare provider for help. For more information on HUMULIN R U-500 KwikPen and insulin, go to www.humulin.com.

Scan this code to launch www.humulin.com

These Instructions for Use have been approved by the U.S. Food and Drug Administration.

HUMULIN® and HUMULIN® KwikPen® are trademarks of Eli Lilly and Company.

Manufactured by:
Eli Lilly and Company
Indianapolis, IN 46285, USA
US License Number 1891

Copyright © 2015, 2022, Eli Lilly and Company. All rights reserved.

HUMULIN R U-500 KwikPen meets the current dose accuracy and functional requirements of ISO 11608-1.

Document revision date: June 2022

LINR500KP-0005-IFU-20220627

VIAL PACKAGE CARTON – HUMULIN R U-500 Vial 20 mL 1ct

NDC 0002-8501-01

20 mL

Humulin® R U-500

(insulin human)
injection

10,000 units per 20 mL

500 units per mL

Rx only

500 units/mL

Warning - Highly Concentrated

IMPORTANT: Use only with a U-500 syringe.

20 mL multiple-dose vial

For subcutaneous use only

www.humulin.com

Lilly

KWIKPEN PACKAGE CARTON – HUMULIN R U-500 KwikPen 3 mL (500 Units per mL)

Dispense in this sealed carton

NDC 0002-8824-27

Humulin®R U-500
KwikPen®

(insulin human)
injection

For Single Patient Use Only

prefilled insulin delivery device

500 units/mL

500 units per mL

2 x 3 mL prefilled pens

Rx only

For subcutaneous use only.

Read Humulin®R U-500 KwikPen® Instructions for Use.

NEEDLES NOT INCLUDED

This device is recommended for use with Becton, Dickinson and Company's insulin pen needles.

DO NOT TRANSFER TO A SYRINGE
SEVERE OVERDOSE CAN RESULT